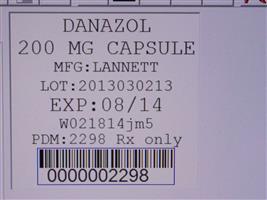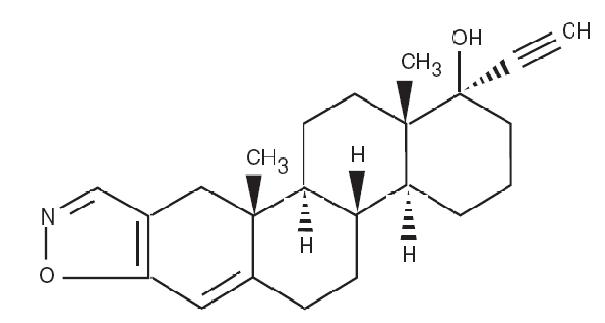 DRUG LABEL: Danazol
NDC: 68151-2298 | Form: CAPSULE
Manufacturer: Carilion Materials Management
Category: prescription | Type: HUMAN PRESCRIPTION DRUG LABEL
Date: 20120126

ACTIVE INGREDIENTS: DANAZOL 200 mg/1 1
INACTIVE INGREDIENTS: ANHYDROUS LACTOSE; LACTOSE MONOHYDRATE; MAGNESIUM STEARATE; STARCH, CORN; SODIUM LAURYL SULFATE; TALC; D&C YELLOW NO. 10; FD&C RED NO. 40; D&C RED NO. 28; GELATIN; TITANIUM DIOXIDE; SHELLAC; ALCOHOL; FERROSOFERRIC OXIDE; BUTYL ALCOHOL; PROPYLENE GLYCOL; METHYL ALCOHOL; FD&C BLUE NO. 2; FD&C BLUE NO. 1; ALUMINUM OXIDE

DANAZOL CAPSULES, USP Rx only

DESCRIPTION

Danazol is a synthetic steroid derived from ethisterone. It is a white to pale yellow crystalline powder, practically insoluble or insoluble in water, and sparingly soluble in alcohol. Chemically, danazol is 17α-Pregna-2, 4-dien-20-yno [2, 3- ]-isoxazol-17-ol. The molecular formula is C H NO . It has a molecular weight of 337.46 and the following structural formula: d22272

Danazol capsules for oral administration contain 50 mg, 100 mg, or 200 mg danazol.

anhydrous lactose, lactose monohydrate, magnesium stearate, pregelatinized starch, sodium lauryl sulfate, talc. Capsule shells for 200 mg danazol contain D&C Yellow #10, FD&C Red #40, D&C Red #28, gelatin, and titanium dioxide. Capsule shells for 50 mg and 100 mg danazol contain D&C Yellow # 10, FD&C Red # 40, gelatin, and titanium dioxide. The capsule imprinting ink contains: shellac glaze in ethanol, iron oxide black, n-butyl alcohol, propylene glycol, ethanol, methanol, FD&C Blue No. 2 Aluminum Lake, FD&C Red No. 40 Aluminum Lake, FD&C Blue No. 1 Aluminum Lake, and D&C Yellow No. 10 Aluminum Lake. Inactive Ingredients:

CLINICAL PHARMACOLOGY

Danazol suppresses the pituitary-ovarian axis. This suppression is probably a combination of depressed hypothalamic-pituitary response to lowered estrogen production, the alteration of sex steroid metabolism, and interaction of danazol with sex hormone receptors. The only other demonstrable hormonal effect is weak androgenic activity. Danazol depresses the output of both follicle-stimulating hormone (FSH) and luteinizing hormone (LH).

Recent evidence suggests a direct inhibitory effect at gonadal sites and a binding of danazol to receptors of gonadal steroids at target organs. In addition, danazol has been shown to significantly decrease IgG, IgM and IgA levels, as well as phospholipid and IgG isotope autoantibodies in patients with endometriosis and associated elevations of autoantibodies, suggesting this could be another mechanism by which it facilitates regression of the disease.

In the treatment of endometriosis, danazol alters the normal and ectopic endometrial tissue so that it becomes inactive and atrophic. Complete resolution of endometrial lesions occurs in the majority of cases.

Changes in vaginal cytology and cervical mucus reflect the suppressive effect of danazol on the pituitary-ovarian axis.

In the treatment of fibrocystic breast disease, danazol usually produces partial to complete disappearance of nodularity and complete relief of pain and tenderness. Changes in the menstrual pattern may occur.

Generally, the pituitary-suppressive action of danazol is reversible. Ovulation and cyclic bleeding usually return within 60 to 90 days when therapy with danazol is discontinued.

In the treatment of hereditary angioedema, danazol at effective doses prevents attacks of the disease characterized by episodic edema of the abdominal viscera, extremities, face, and airway which may be disabling and, if the airway is involved, fatal. In addition, danazol corrects partially or completely the primary biochemical abnormality of hereditary angioedema by increasing the levels of the deficient C1 esterase inhibitor (C1El). As a result of this action the serum levels of the C4 component of the complement system are also increased.

Pharmacokinetics

Absorption: After oral administration of a 400 mg dose to healthy male volunteers, peak plasma concentrations of danazol are reached between 2 and 8 hours, with a median T value of 4 hours. Steady state conditions are observed following 6 days of twice daily dosing of danazol.max

The pharmacokinetic parameters for danazol after administering a 400 mg oral dose to healthy males are summarized in the following table:

Parameters | Mean ± SD (n=15)
C (ng/mL)max | 69.6 ± 29.9
T (h)max | 2.47 ± 1.62
AUC (ng*h/mL)0-∞ | 601 ± 181
t (h)1/2 | 9.70 ± 3.29
Total Body Clearance (L/h) | 727 ± 221

The pharmacokinetic parameters for danazol after oral administration of 100, 200 and 400 mg single doses to healthy female volunteers are summarized in the following table:

Dose (mg) | Mean C ± (max SD ng/mL) |  | Mean T (h)max |  | Mean AUC ± SD (0-∞ ng*h/mL)
 | Fasting | Fed | Fasting | Fed | Fasting | Fed
100 | 45.9 ±23.9 | 113.8 ± 46.0 | 1-8 | 2-6 | 484 ± 263 | 741 ± 265
200 | 63.8 ± 27.7 | 159 ± 57.3 | 1-6 | 2-4 | 681 ± 363 | 1252 ± 307
400 | 60.4 ± 30.0 | 253.7 ± 105.5 | 1-6 | 2-4 | 754 ± 443 | 1851 ± 605

Bioavailability studies indicate that blood levels do not increase proportionally with increases in the administered dose. Dose proportionality:

Single dose administration of danazol in healthy female volunteers found that a 4-fold increase in dose produced only a 1.6 and 2.5-fold increase in AUC and a 1.3 and 2.2-fold increase in C in the fasted and fed state, respectively. A similar degree of non-dose proportionality was observed at steady state.max

Single dose administration of 100 mg and 200 mg capsules of danazol to female volunteers showed that both the extent of availability and the maximum plasma concentration increased by 3 to 4 fold, respectively, following a meal (> 30 grams of fat), when compared to the fasted state. Further, food also delayed mean time to peak concentration of danazol by about 30 minutes. Even after multiple dosing under less extreme food/fasting conditions, there remained approximately a 2 to 2.5 fold difference in bioavailability between the fed and fasted states. Food Effect:

Distribution: Danazol is lipophilic and can partition into cell membranes, indicating the likelihood of distribution into deep tissue compartments.

Metabolism and Excretion: Danazol appears to be metabolized and the metabolites are eliminated by renal and fecal pathways. The two primary metabolites excreted in the urine are 2-hydroxymethyl danazol and ethisterone. At least ten different products were identified in feces.

The reported elimination half-life of danazol is variable across studies. The mean half-life of danazol in healthy males is 9.7 h. After 6 months of 200 mg three times a day dosing in endometriosis patients, the half-life of danazol was reported as 23.7 hours.

INDICATIONS AND USAGE

Endometriosis

Danazol capsules are indicated for the treatment of endometriosis amenable to hormonal management.

Fibrocystic Breast Disease

Most cases of symptomatic fibrocystic breast disease may be treated by simple measures (e.g., padded brassieres and analgesics).

In infrequent patients, symptoms of pain and tenderness may be severe enough to warrant treatment by suppression of ovarian function. Danazol capsules are usually effective in decreasing nodularity, pain, and tenderness. It should be stressed to the patient that this treatment is not innocuous in that it involves considerable alterations of hormone levels and that recurrence of symptoms is very common after cessation of therapy.

Hereditary Angioedema

Danazol capsules are indicated for the prevention of attacks of angioedema of all types (cutaneous, abdominal, laryngeal) in males and females.

CONTRAINDICATIONS

Danazol capsules should not be administered to patients with:

1. Undiagnosed abnormal genital bleeding.
2. Markedly impaired hepatic, renal, or cardiac function.
3. Pregnancy (see). WARNINGS
4. Breast feeding.
5. Porphyria - danazol can induce ALA synthetase activity and hence porphyrin metabolism.
6. Androgen-dependent tumor.
7. Active thrombosis or thromboembolic disease and history of such events.
8. Hypersensitivity to danazol.

WARNINGS

BOXED WARNING

Use of danazol in pregnancy is contraindicated. A sensitive test (e.g., beta subunit test if available) capable of determining early pregnancy is recommended immediately prior to start of therapy. Additionally a non-hormonal method of contraception should be used during therapy. If a patient becomes pregnant while taking danazol, administration of the drug should be discontinued and the patient should be apprised of the potential risk to the fetus. Exposure to danazol in utero may result in androgenic effects on the female fetus; reports of clitoral hypertrophy, labial fusion, urogenital sinus defect, vaginal atresia, and ambiguous genitalia have been received. (See .) PRECAUTIONS: Pregnancy, Teratogenic Effects

Thromboembolism, thrombotic and thrombophlebitic events including sagittal sinus thrombosis and life-threatening or fatal strokes have been reported.

Experience with long-term therapy with danazol is limited. Peliosis hepatis and benign hepatic adenoma have been observed with long-term use. Peliosis hepatis and hepatic adenoma may be silent until complicated by acute, potentially life-threatening intraabdominal hemorrhage. The physician therefore should be alert to this possibility. Attempts should be made to determine the lowest dose that will provide adequate protection. If the drug was begun at a time of exacerbation of hereditary angioneurotic edema due to trauma, stress or other cause, periodic attempts to decrease or withdraw therapy should be considered.

Danazol has been associated with several cases of benign intracranial hypertension also known as pseudotumor cerebri. Early signs and symptoms of benign intracranial hypertension include papilledema, headache, nausea and vomiting, and visual disturbances. Patients with these symptoms should be screened for papilledema and, if present, the patients should be advised to discontinue danazol immediately and be referred to a neurologist for further diagnosis and care.

A temporary alteration of lipoproteins in the form of decreased high density lipoproteins and possibly increased low density lipoproteins has been reported during danazol therapy. These alterations may be marked, and prescribers should consider the potential impact on the risk of atherosclerosis and coronary artery disease in accordance with the potential benefit of the therapy to the patient.

Before initiating therapy of fibrocystic breast disease with danazol, carcinoma of the breast should be excluded. However, nodularity, pain, tenderness due to fibrocystic breast disease may prevent recognition of underlying carcinoma before treatment is begun. Therefore, if any nodule persists or enlarges during treatment, carcinoma should be considered and ruled out.

Patients should be watched closely for signs of androgenic effects some of which may not be reversible even when drug administration is stopped.

PRECAUTIONS

Because danazol may cause some degree of fluid retention, conditions that might be influenced by this factor, such as epilepsy, migraine, or cardiac or renal dysfunction, polycythemia and hypertension require careful observation. Use with caution in patients with diabetes mellitus.

Since hepatic dysfunction manifested by modest increases in serum transaminases levels has been reported in patients treated with danazol, periodic liver function tests should be performed (see and). WARNINGSADVERSE REACTIONS

Administration of danazol has been reported to cause exacerbation of the manifestations of acute intermittent porphyria. (See .) CONTRAINDICATIONS

Laboratory monitoring of the hematologic state should be considered.

Drug Interactions

Prolongation of prothrombin time occurs in patients stabilized on warfarin.

Therapy with danazol may cause an increase in carbamazepine levels in patients taking both drugs.

Danazol can cause insulin resistance. Caution should be exercised when used with antidiabetic drugs.

Danazol may raise the plasma levels of cyclosporin and tacrolimus, leading to an increase of the renal toxicity of these drugs. Monitoring of systemic concentrations of these drugs and appropriate dose adjustments may be needed when used concomitantly with danazol.

Danazol can increase the calcemic response to synthetic vitamin D analogs in primary hypoparathyroidism.

The risk of myopathy and rhabdomyolysis is increased by concomitant administration of danazol with statins such as simvastatin, atorvastatin and lovastatin. Caution should be exercised if used concomitantly. Consult the product labeling for statin drugs for specific information on dose restrictions in presence of danazol.

Laboratory Tests

Danazol treatment may interfere with laboratory determinations of testosterone, androstenedione and dehydroepiandrosterone. Other metabolic events include a reduction in thyroid binding globulin and T4 with increased uptake of T3, but without disturbance of thyroid stimulating hormone or of free thyroxin index.

Carcinogenesis, Mutagenesis, Impairment of Fertility

Current data are insufficient to assess the carcinogenicity of danazol.

Pregnancy

Teratogenic Effects

(See .) CONTRAINDICATIONS

Pregnancy Category X

Danazol administered orally to pregnant rats from the 6th through the 15th day of gestation at doses up to 250 mg/kg/day (7-15 times the human dose) did not result in drug-induced embryotoxicity or teratogenicity, nor difference in litter size, viability or weight of offspring compared to controls. In rabbits, the administration of danazol on days 6-18 of gestation at doses of 60 mg/kg/day and above (2-4 times the human dose) resulted in inhibition of fetal development.

Nursing Mothers

(See). CONTRAINDICATIONS

Pediatric Use

Safety and effectiveness in pediatric patients have not been established.

Geriatric Use

Clinical studies of danazol did not include sufficient numbers of subjects aged 65 and over to determine the safety and effectiveness of danazol in elderly patients.

ADVERSE REACTIONS

The following events have been reported in association with the use of danazol:

Androgen like effects include weight gain, acne and seborrhea. Mild hirsutism, edema, hair loss, voice change, which may take the form of hoarseness, sore throat or of instability or deepening of pitch, may occur and may persist after cessation of therapy. Hypertrophy of the clitoris is rare.

Other possible endocrine effects are menstrual disturbances including spotting, alteration of the timing of the cycle and amenorrhea. Although cyclical bleeding and ovulation usually return within 60-90 days after discontinuation of therapy with danazol, persistent amenorrhea has occasionally been reported.

Flushing, sweating, vaginal dryness and irritation and reduction in breast size, may reflect lowering of estrogen. Nervousness and emotional lability have been reported. In the male a modest reduction in spermatogenesis may be evident during treatment. Abnormalities in semen volume, viscosity, sperm count, and motility may occur in patients receiving long-term therapy.

Hepatic dysfunction, as evidenced by reversible elevated serum enzymes and/or jaundice, has been reported in patients receiving a daily dosage of danazol of 400 mg or more. It is recommended that patients receiving danazol be monitored for hepatic dysfunction by laboratory tests and clinical observation. Serious hepatic toxicity including cholestatic jaundice, peliosis hepatis, and hepatic adenoma have been reported (see and). WARNINGSPRECAUTIONS

Abnormalities in laboratory tests may occur during therapy with danazol including CPK, glucose tolerance, glucagon, thyroid binding globulin, sex hormone binding globulin, other plasma proteins, lipids and lipoproteins.

The following reactions have been reported, a causal relationship to the administration of danazol has neither been confirmed nor refuted; urticaria, pruritus and rarely, nasal congestion; headache, nervousness and emotional lability, dizziness and fainting, depression, fatigue, sleep disorders, tremor, paresthesias, weakness, visual disturbances, and rarely, benign intracranial hypertension, anxiety, changes in appetite, chills, and rarely convulsions, Guillain-Barre syndrome; gastroenteritis, nausea, vomiting, constipation, and rarely, pancreatitis and splenic peliosis; muscle cramps or spasms, or pains, joint pain, joint lockup, joint swelling, pain in back, neck, or extremities, and rarely, carpal tunnel syndrome which may be secondary to fluid retention; hematuria, prolonged posttherapy amenorrhea; an increase in red cell and platelet count. Reversible erythrocytosis, leukocytosis or polycythemia may be provoked. Eosinophilia, leukopenia and thrombocytopenia have also been noted. rashes (maculopapular, vesicular, papular, purpuric, petechial), and rarely, sun sensitivity, Stevens-Johnson syndrome and erythema multiforme; increased insulin requirements in diabetic patients, change in libido, myocardial infarction, palpitation, tachycardia, elevation in blood pressure,interstitial pneumonitis, and rarely, cataracts, bleeding gums, fever, pelvic pain, nipple discharge. Malignant liver tumors have been reported in rare instances, after long-term use. allergic: CNS effects: gastrointestinal: musculoskeletal: genitourinary: hematologic: Skin: other:

DOSAGE AND ADMINISTRATION

Endometriosis

In moderate to severe disease, or in patients infertile due to endometriosis, a starting dose of 800 mg given in two divided doses is recommended. Amenorrhea and rapid response to painful symptoms is best achieved at this dosage level. Gradual downward titration to a dose sufficient to maintain amenorrhea may be considered depending upon patient response. For mild cases, an initial daily dose of 200 mg to 400 mg given in two divided doses is recommended and may be adjusted depending on patient response. After termination of therapy, if symptoms recur, treatment can be reinstituted. Therapy should begin during menstruation. Otherwise, appropriate tests should be performed to ensure that the patient is not pregnant while on therapy with danazol (see and). It is essential that therapy continue uninterrupted for 3 to 6 months but may be extended to 9 months if necessary. CONTRAINDICATIONSWARNINGS

Fibrocystic Breast Disease

The total daily dosage of danazol for fibrocystic breast disease ranges from 100 mg to 400 mg given in two divided doses depending upon patient response. A nonhormonal method of contraception is recommended when danazol is administered at this dose, since ovulation may not be suppressed. Therapy should begin during menstruation. Otherwise, appropriate tests should be performed to ensure that the patient is not pregnant while on therapy with danazol.

In most instances, breast pain and tenderness are significantly relieved by the first month and eliminated in 2 to 3 months. Usually elimination of nodularity requires 4 to 6 months of uninterrupted therapy. Regular menstrual patterns, irregular menstrual patterns, and amenorrhea each occur in approximately one-third of patients treated with 100 mg of danazol. Irregular menstrual patterns and amenorrhea are observed more frequently with higher doses. Clinical studies have demonstrated that 50% of patients may show evidence of recurrence of symptoms within one year. In this event, treatment may be reinstated.

Hereditary Angioedema

The dosage requirements for continuous treatment of hereditary angioedema with danazol should be individualized on the basis of the clinical response of the patient. It is recommended that the patient be started on 200 mg, two or three times a day. After a favorable initial response is obtained in terms of prevention of episodes of edematous attacks, the proper continuing dosage should be determined by decreasing the dosage by 50% or less at intervals of one to three months or longer if frequency of attacks prior to treatment dictates. If an attack occurs, the daily dosage may be increased by up to 200 mg. During the dose adjusting phase, close monitoring of the patient's response is indicated, particularly if the patient has a history of airway involvement.

HOW SUPPLIED

NDC:68151-2298-0 in a PACKAGE of 1 CAPSULES